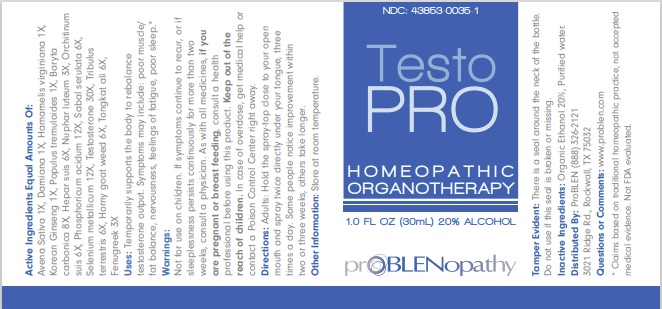 DRUG LABEL: TestoPRO
NDC: 43853-0035 | Form: SPRAY
Manufacturer: ProBlen
Category: homeopathic | Type: HUMAN OTC DRUG LABEL
Date: 20221130
DEA Schedule: CIII

ACTIVE INGREDIENTS: SUS SCROFA TESTICLE 6 [hp_X]/30 mL; PHOSPHORIC ACID 12 [hp_X]/30 mL; SAW PALMETTO 6 [hp_X]/30 mL; SELENIUM 12 [hp_X]/30 mL; TESTOSTERONE 30 [hp_X]/30 mL; TRIBULUS TERRESTRIS WHOLE 6 [hp_X]/30 mL; EPIMEDIUM GRANDIFLORUM TOP 6 [hp_X]/30 mL; EURYCOMA LONGIFOLIA WHOLE 6 [hp_X]/30 mL; FENUGREEK SEED 3 [hp_X]/30 mL; AVENA SATIVA FLOWERING TOP 1 [hp_X]/30 mL; TURNERA DIFFUSA LEAFY TWIG 1 [hp_X]/30 mL; HAMAMELIS VIRGINIANA ROOT BARK/STEM BARK 1 [hp_X]/30 mL; ASIAN GINSENG 1 [hp_X]/30 mL; POPULUS TREMULOIDES WHOLE 1 [hp_X]/30 mL; BARIUM CARBONATE 8 [hp_X]/30 mL; PORK LIVER 6 [hp_X]/30 mL; NUPHAR LUTEA ROOT 3 [hp_X]/30 mL
INACTIVE INGREDIENTS: ALCOHOL; WATER

TestoPRO

Active Ingredients Equal Amounts Of:
Avena Sativa 1X, Damiana 1X, Hamamelis virginiana 1X, Korean Ginseng 1X, Populus tremuloides 1X, Baryta
carbonica 8X, Hepar suis 6X, Nuphar luteum 3X, Orchitinum suis 6X, Phosphoricum acidum 12X, Sabal serulata 6X,
Selenium metallicum 12X, Testosterone 30X, Tribulus terrestris 6X, Horny goat weed 6X, Tongkat ali 6X, Fenugreek 3X

* Claims based on traditional homeopathic practice, not accepted medical evidence. Not FDA evaluated.

INDICATIONS AND USAGE

Uses: Temporarily supports the body to rebalance testosterone output. Symptoms may include: poor muscle/ fat balance, nervousness, feelings of fatigue, poor sleep.*

Warnings:

Not for use on children. If symptoms continue to recur, or if sleeplessness persists continuously for more than two weeks, consult a physician. As with all medicines, if you are pregnant or breast feeding, consult a health professional before using this product. Keep out of the reach of children. In case of overdose, get medical help or contact a Poison Control Center right away.

Keep out of the reach of children.

DOSAGE AND ADMINISTRATION

Directions: Adults: Hold the spray-top close to your open mouth and spray twice directly under your tongue, three times a day. Some people notice improvement within two or three weeks, others take longer.

Other Information: Store at room temperature.

Tamper Evident: There is a seal around the neck of the bottle. Do not use if this seal is broken or missing.

Inactive Ingredients: Organic Ethanol 20%, Purified water.

QUESTIONS

Distributed By: ProBLEN (888) 326-2121 3021 Ridge Rd., Rockwall, TX 75032

Questions or Comments: www.problen.com

PACKAGE LABEL

NDC: 43853-0035-1

TestoPRO

HOMEOPATHIC

ORGANOTHERAPY

1.0 FL OZ (30mL) 20% ALCOHOL

prOBLENopathy

PURPOSE

Temporarily supports the body to rebalance testosterone output.